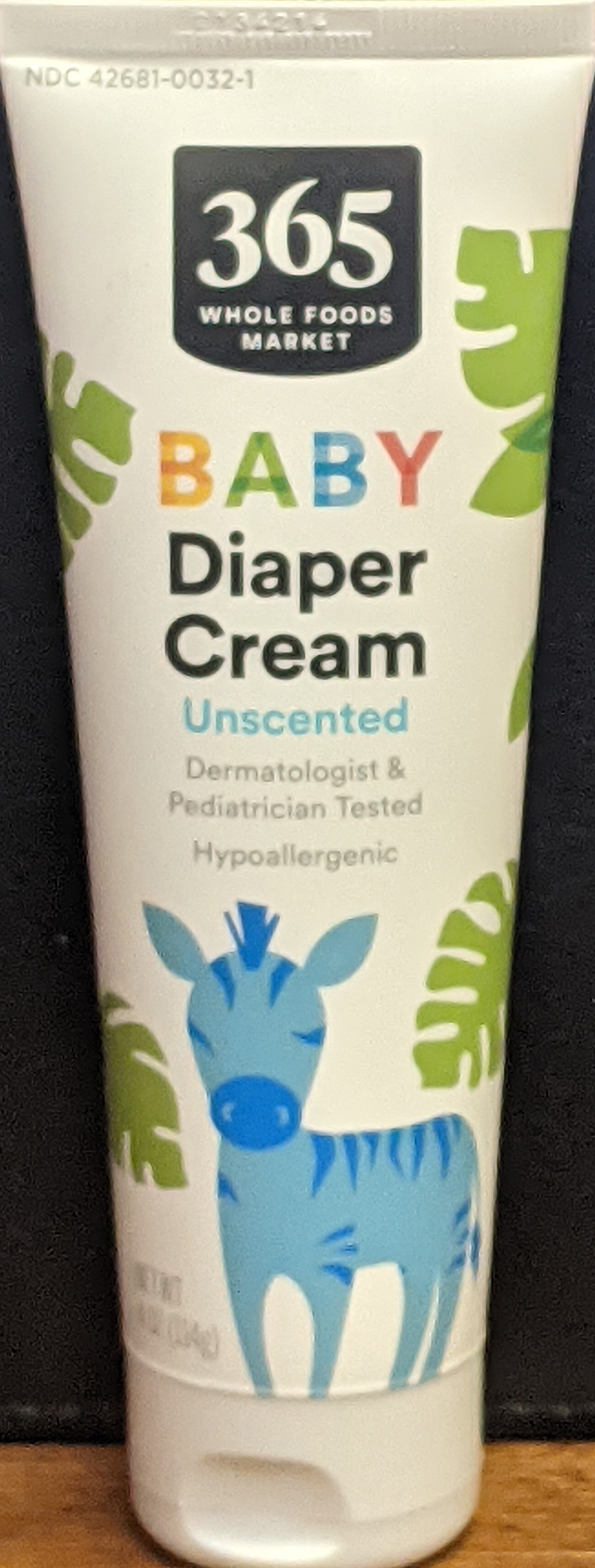 DRUG LABEL: BabyDiaperCream
NDC: 42681-0032 | Form: CREAM
Manufacturer: Whole Foods Market
Category: otc | Type: HUMAN OTC DRUG LABEL
Date: 20250429

ACTIVE INGREDIENTS: ZINC OXIDE 14 g/100 g
INACTIVE INGREDIENTS: WATER 37 g/100 g

Baby Diaper Cream

Active Ingredients

Zinc Oxide 14.0% ……………………………………….. Skin Protectant

Purpose:

Skin Protectant

Uses:

Helps treat and prevent diaper rash. ■Helps protect against chafed skin due to diaper rash and helps seal out wetness.

Warnings:

■For external use only ■When using this product do not get into eyes. ■Stop use and ask a doctor if condition worsens, symptoms last more than 7 days, or clear up and occur again within a few days. ■Keep out of the reach of children. If swallowed, seek medical help or contact a Poison Control Center immediately.

Directions:

■Change wet and soiled diapers promptly. ■Cleanse diaper area and allow to dry. ■Apply diaper cream liberally and as often as necessary to prevent or treat irritation, with each diaper change.

Storage

Store in a cool, dry place

Inactive Ingredients:

Aloe Barbadensis Leaf Juice, Avena Sativa (Oat) Kernel Extract, Avena Sativa (Oat) Kernel Flour, Beeswax, Benzyl Alcohol, Bisabolol, Butyrospermum Parkii (Shea) Butter, Caprylic/Capric Triglyceride, Carthamus Tinctorius (Safflower) Seed Oil, Cetearyl Alcohol, Echinacea Purpurea Extract, Geranium Maculatum Extract, Gluconolactone, Glycerin, Glyceryl Isostearate, Glyceryl Stearate, Glyceryl Stearate SE, Hydroxyethyl Acrylate/Sodium Acryloyldimethyl Taurate Copolymer, Hydroxyethylcellulose, Kaolin, PEG-100 Stearate, Phenoxyethanol, Polyhydroxystearic Acid, Polysorbate 60, Ricinus Communis (Castor) Seed Oil, Squalane, Tocopheryl Acetate, Water (Aqua).

Questions, Comments?

■ Questions, Comments: 1-844-WFM-TALK (1-844-936-8255)

Usage:

Helps treat and prevent diaper rash. Helps protect against chafed skin due to diaper rash and helps seal out wetness.

Keep out of reach of children.